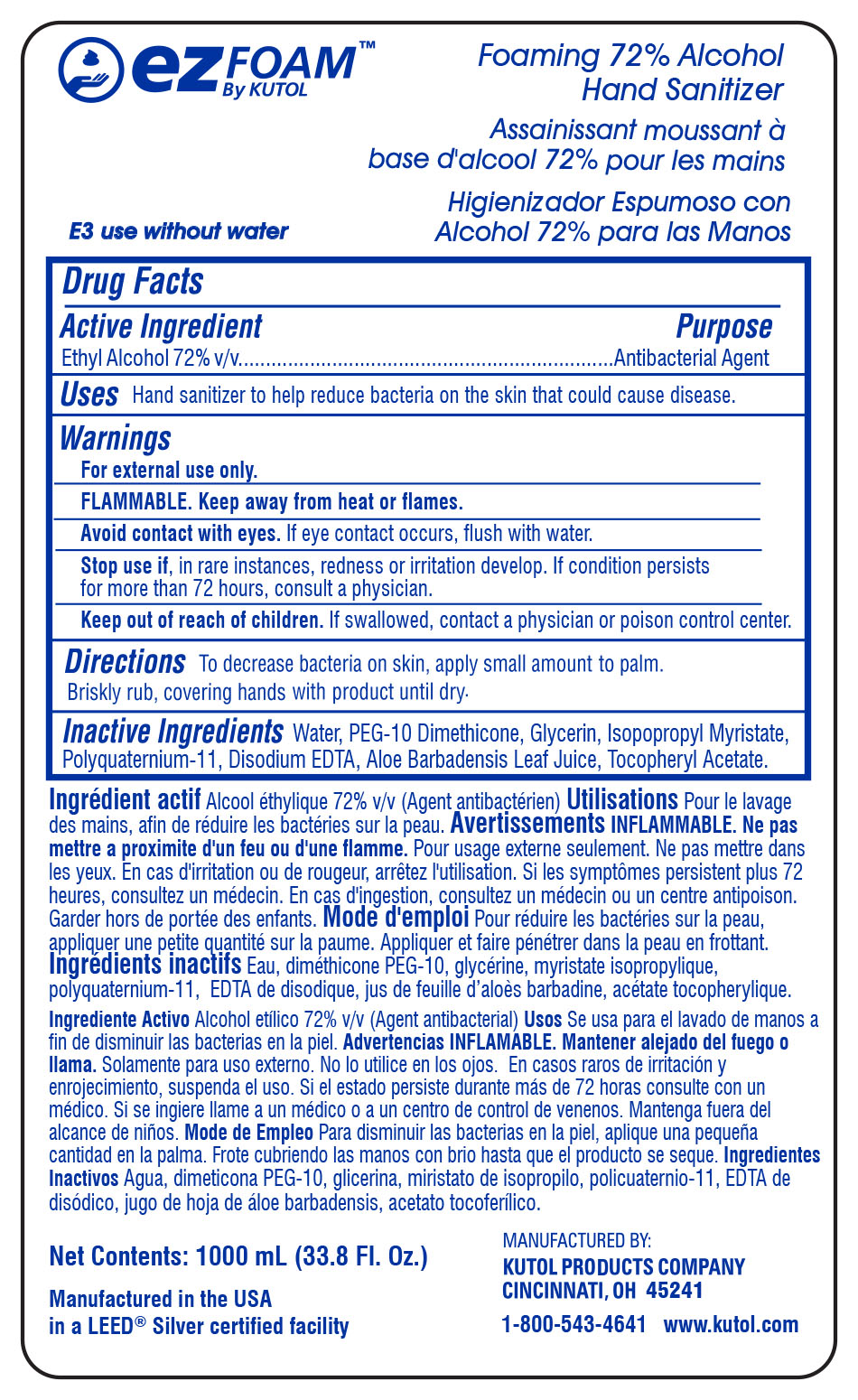 DRUG LABEL: Foaming Sanitizing Hand
NDC: 50865-710 | Form: SOAP
Manufacturer: Kutol Products Company
Category: otc | Type: HUMAN OTC DRUG LABEL
Date: 20241218

ACTIVE INGREDIENTS: ALCOHOL 0.072 mg/1 mL
INACTIVE INGREDIENTS: ALOE VERA LEAF; WATER; PEG-10 DIMETHICONE (600 CST); EDETATE DISODIUM; GLYCERIN; ISOPROPYL MYRISTATE; POLYQUATERNIUM-11 (1000000 MW); .ALPHA.-TOCOPHEROL ACETATE

F710F

Active Ingredient

Ethyl Alcohol 72% v/v

Purpose

Antibacterial

Keep out of reach of children. If swallowed, contact a physician or poison control center.

INDICATIONS AND USAGE

Uses Hand sanitizer to help reduce bacteria on the skin that could cause disease.

DOSAGE AND ADMINISTRATION

Directions To decrease bacteria on skin, apply small amount to palm. Briskly rub, covering hands with product until dry.

Warnings

For external use only.

FLAMMABLE. Keep away from heat or flames.

Avoid contact with eyes. If eye contact occurs, flush eyes with water.

Stop use if, in rare instances, redness or irritation develop. If condition persists for more than 72 hours, consult a physician.

Inactive Ingredients

water, cocamidopropyl PG-dimonium chloride phosphate,cocamidopropyl betaine, PEG-6 cocamide, laurtrimonium chloride, iodopropynyl butylcarbamate,methylisothiazolinone.